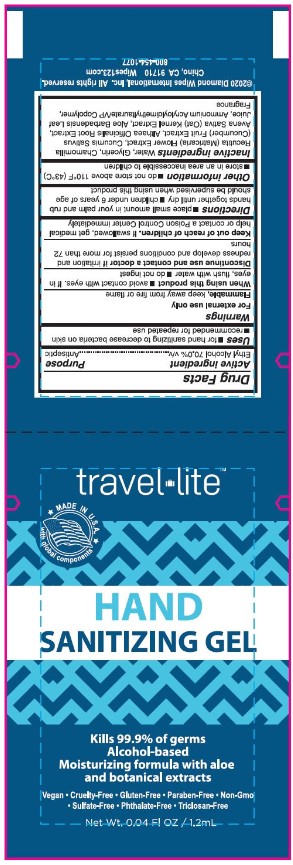 DRUG LABEL: Travel Lite Hand Sanitizing Gel
NDC: 64709-177 | Form: GEL
Manufacturer: Diamond Wipes International, Inc
Category: otc | Type: HUMAN OTC DRUG LABEL
Date: 20231204

ACTIVE INGREDIENTS: ALCOHOL 70 mL/100 mL
INACTIVE INGREDIENTS: OAT; WATER; GLYCERIN; CHAMOMILE; CUCUMBER; ALTHAEA OFFICINALIS ROOT; ALOE VERA LEAF; AMMONIUM ACRYLOYLDIMETHYLTAURATE/VP COPOLYMER

Travel Lite Hand Sanitizing Gel

Active Ingredient(s)

Ethyl Alcohol 70% v/v

Purpose

Antiseptic

Uses

• for hand sanitizing to decrease bacteria on skin

• recommended for repeated use

Warnings

- For external use only
- Flammable, Keep away from heat or flame

When using this product

• avoid contact with eyes. if in eyes, flush with water

• do not ingest

Discontinue use and contact a doctor

if irritation and redness develop and conditions persist for more than 72 hours

Keep out of reach of children.

If swallowed, get medical help or contact a Poison Control Center immediately

Directions

• place small amount in your palm and rub hands together until dry

• children under 6 years of age should be supervised when using this product

Other information

• do not store above 110F (43C)

• store in an area inaccessible to children

Inactive ingredients

Water, Glycerin, Chamomilla Recutita (Matricaria) Flower Extract, Cucumis Sativus (Cucumber) Fruit Extract, Althaea Officinalis Root Extract, Avena Sativa (Oat) Kernel Extract, Aloe Barbadensis Leaf Juice, Ammonium Acryloyldimethyltaurate/VP Copolymer, Fragrance

Label

travel lite TM

MAKE IN U.S.A. with global components

HAND SANITIZING WIPES

kills 99.9% of germs

Alcohol-based

Moisturizing formula with aloe

and botanical extracts

Vegan • Cruelty-Free • Gluten-Free • Non-Gmo

• Sulfate-Free • Phthalate-Free • Triclosan-Free

Net Wt. 0.04Fl OZ / 1.2mL

©2020 Diamond Wipes International, Inc. All rights reserved.

Chino, CA91710 Wipes123.com

800-454-1077